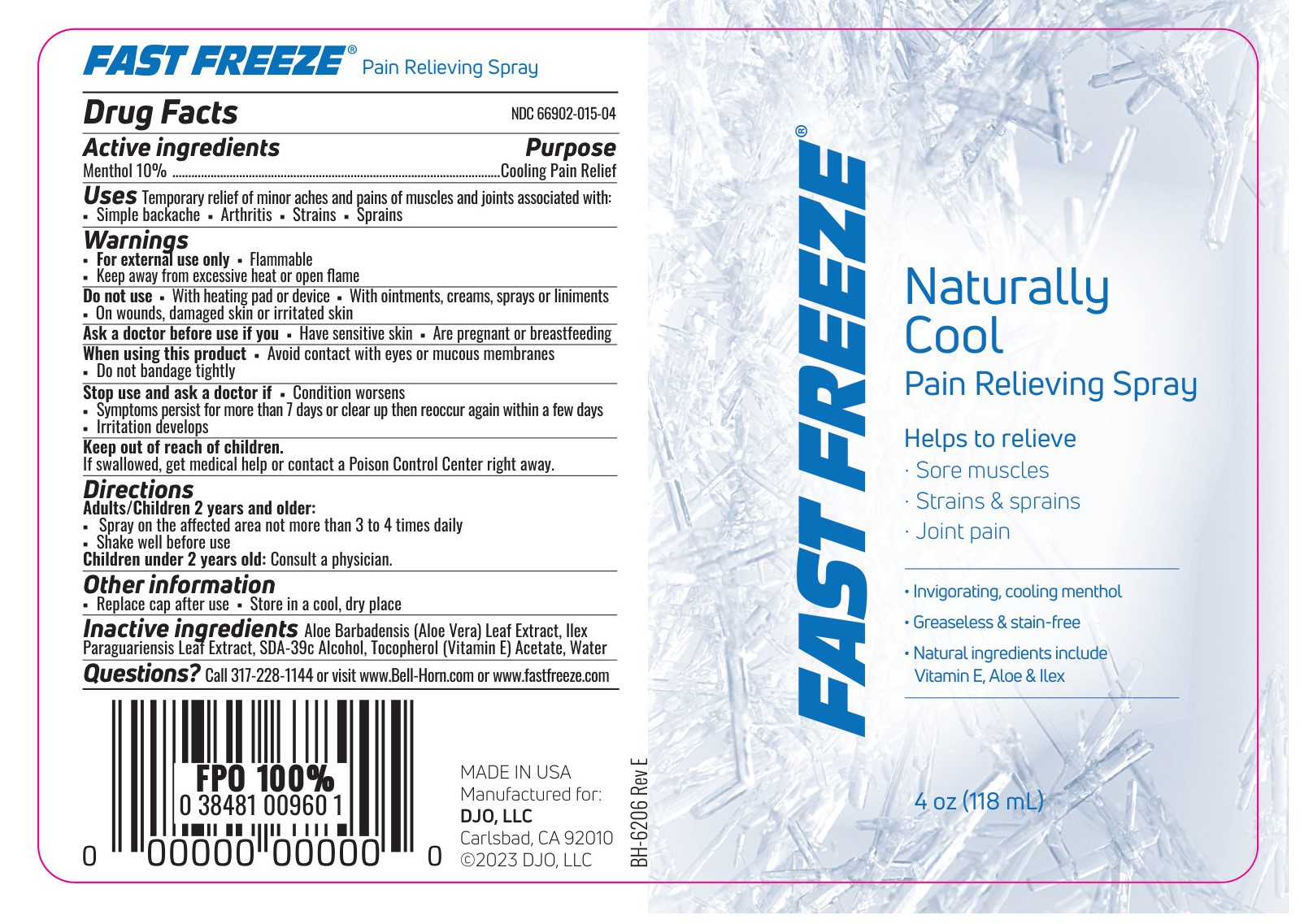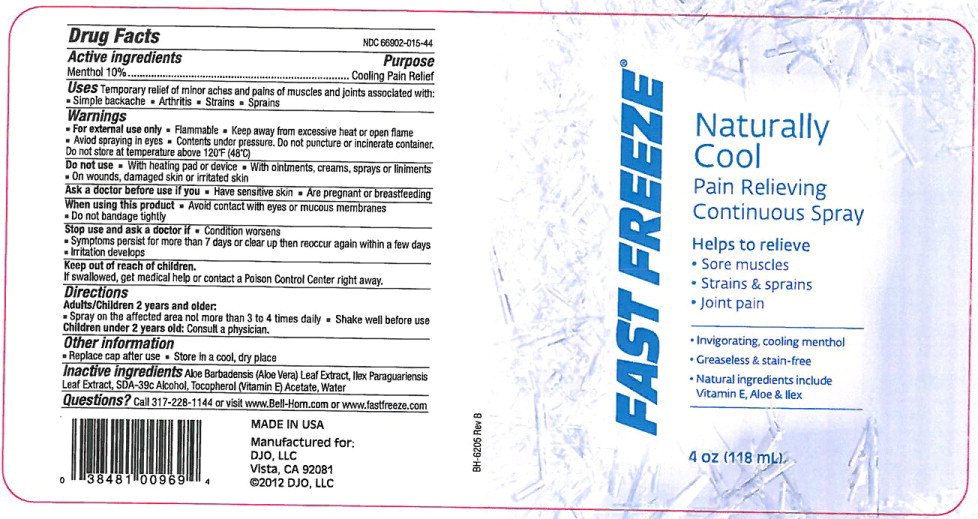 DRUG LABEL: Fast Freeze
NDC: 66902-015 | Form: SPRAY
Manufacturer: Natural Essentials Inc.
Category: otc | Type: HUMAN OTC DRUG LABEL
Date: 20250812

ACTIVE INGREDIENTS: MENTHOL 100 mg/1 mL
INACTIVE INGREDIENTS: ALOE VERA LEAF; ILEX PARAGUARIENSIS LEAF; ISOPROPYL ALCOHOL; .ALPHA.-TOCOPHEROL ACETATE; WATER

Fast Freeze NDC 66902-015

Drug Facts

Active ingredients

Menthol 10%

Purpose

Cooling Pain Relief

Uses

Temporary relief of minor aches and pains of muscles and joints associated with:

- Simple backache
- Arthritis
- Strains
- Sprains

Warnings

- For external use only
- Flammable
- Keep away from excessive heat or open flame
- Avoid spraying in eyes
- Contents under pressure. Do not puncture or incinerate container. Do not store at temperature above 120°F (48°C)

Do not use

- With heating pad or device
- With ointments, creams, sprays or liniments
- On wounds, damaged skin or irritated skin

Ask a doctor before use if you

- Have sensitive skin
- Are pregnant or breastfeeding

When using this product

- Avoid contact with eyes or mucous membranes
- Do not bandage tightly

Stop use and ask a doctor if

- Condition worsens
- Symptoms persist for more than 7 days or clear up then reoccur again within a few days
- Irritation develops

Keep out of reach of children.

If swallowed, get medical help or contact a Poison Control Center right away.

Directions

Adults/Children 2 years and older:

- Spray on the affected area not more than 3 to 4 times daily
- Shake well before use

Children under 2 years old:Consult a physician.

Other information

- Replace cap after use
- Store in a cool, dry place

Inactive ingredients

Aloe Barbadensis (Aloe Vera) Leaf Extract, Ilex Paraguariensis Leaf Extract,SDA-39c Alcohol, Tocopherol (Vitamin E) Acetate, Water

Questions?

Call 317-228-1144 or visit www.Bell-Horn.com or www.fastfreeze.com

Principal Display Panel – Bottle Label

FAST FREEZE®

Naturally
Cool

Pain Relieving

Continuous Spray

Helps to relieve

- Sore muscles
- Strains & sprains
- Joint pain

………………………………….

- Invigorating cooling menthol
- Greaseless & stain-free
- Natural ingredients include
  Vitamin E, Aloe & llex

………………………………….

4 oz (118 mL)

Principal Display Panel - Pump Bottle Label 4 oz (118 mL)

Fast Freeze®

Naturally Cool

Pain Relieving Spray

Helps to relieve

- Sore muscles
- Strains & sprains
- Joint Pain

------------------------------____________________________

- Invigorating, cooling menthol
- Greaseless & stain-free
- Natural ingredients include Vitamin E, Aloe & Ilex

_______________________________________________

4 oz (118 mL)